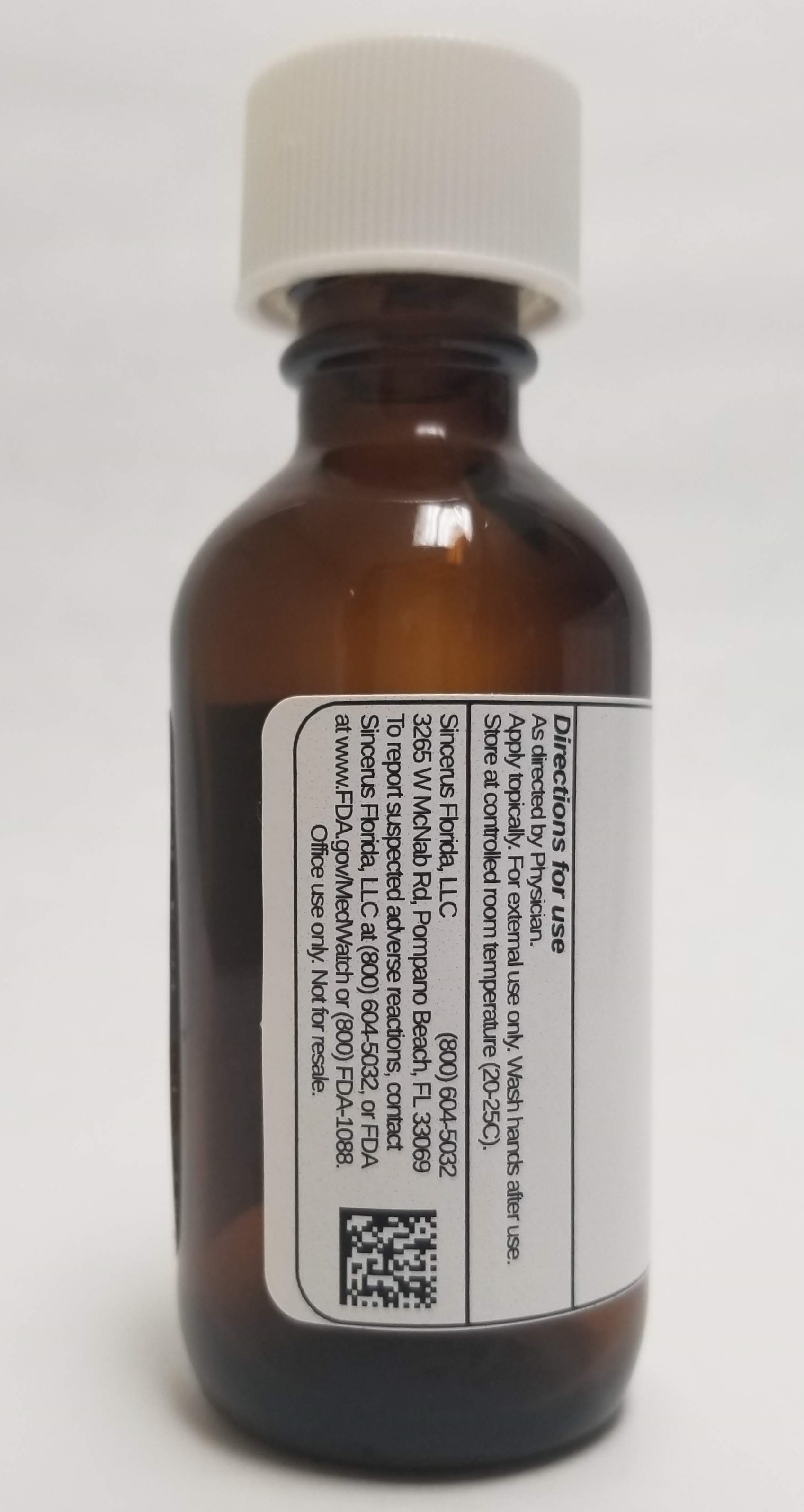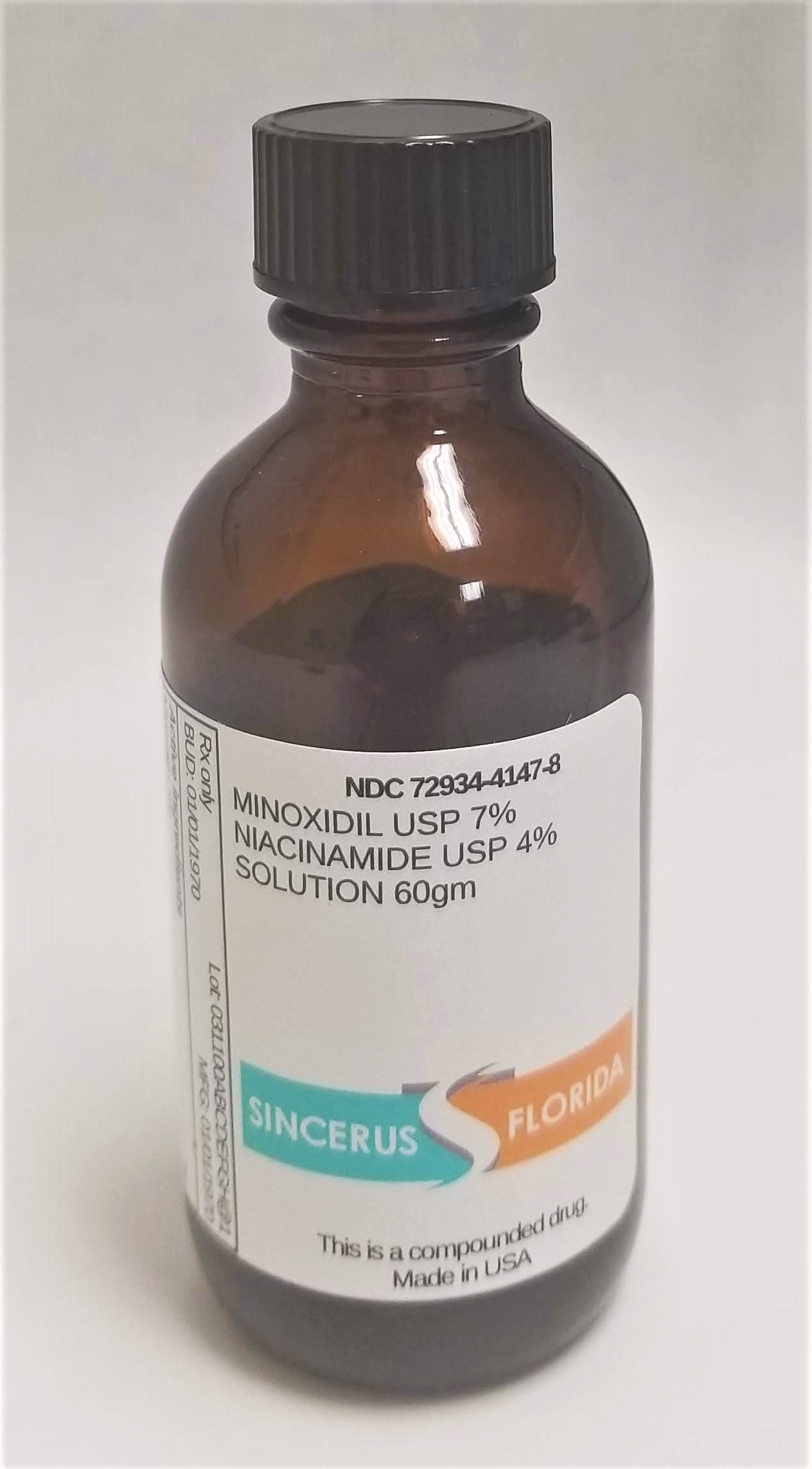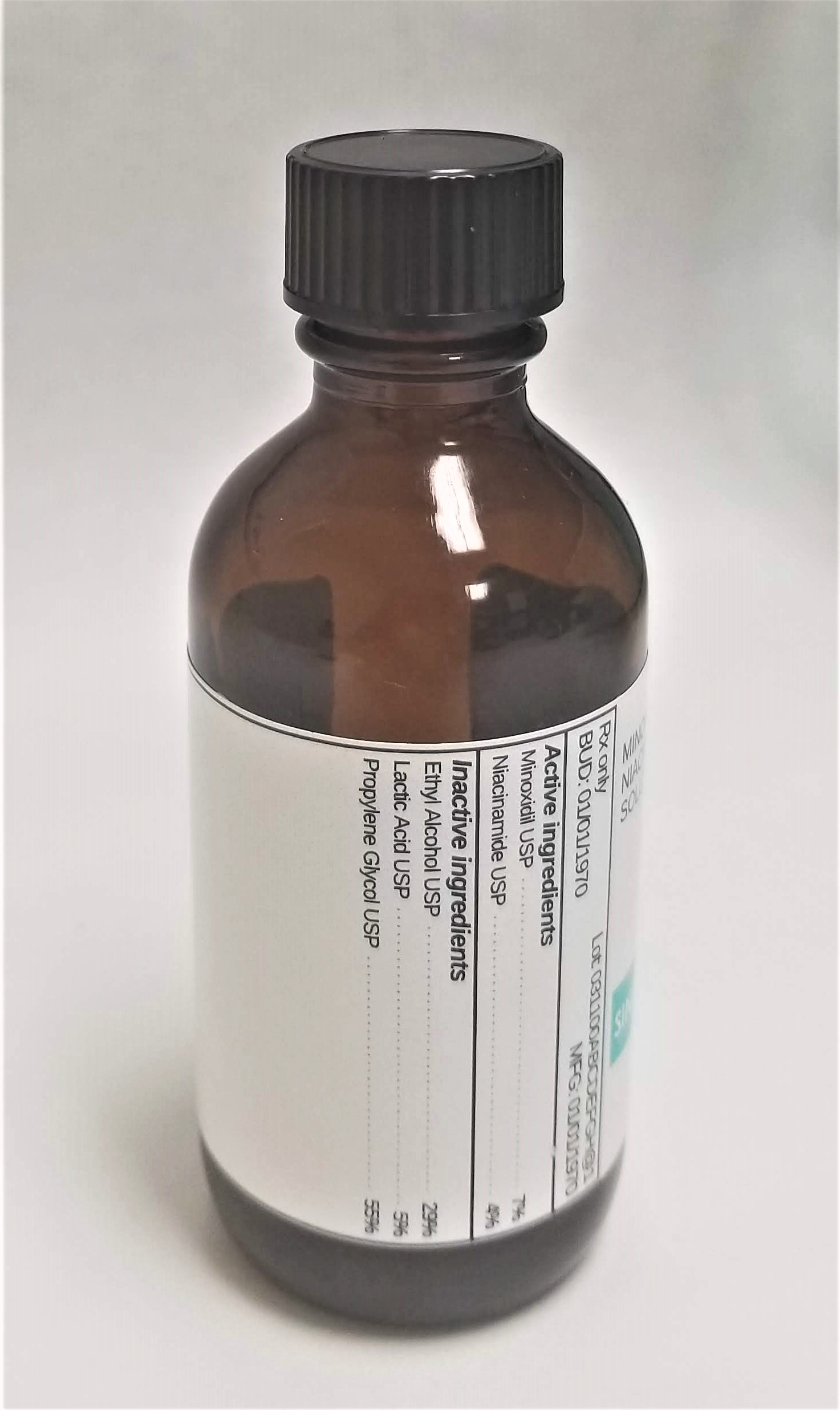 DRUG LABEL: MINOXIDIL 7% / NIACINAMIDE 4%
NDC: 72934-4147 | Form: SOLUTION
Manufacturer: Sincerus Florida, LLC
Category: prescription | Type: HUMAN PRESCRIPTION DRUG LABEL
Date: 20190509

ACTIVE INGREDIENTS: MINOXIDIL 7 g/100 g; NIACINAMIDE 4 g/100 g

MINOXIDIL 7% / NIACINAMIDE 4%